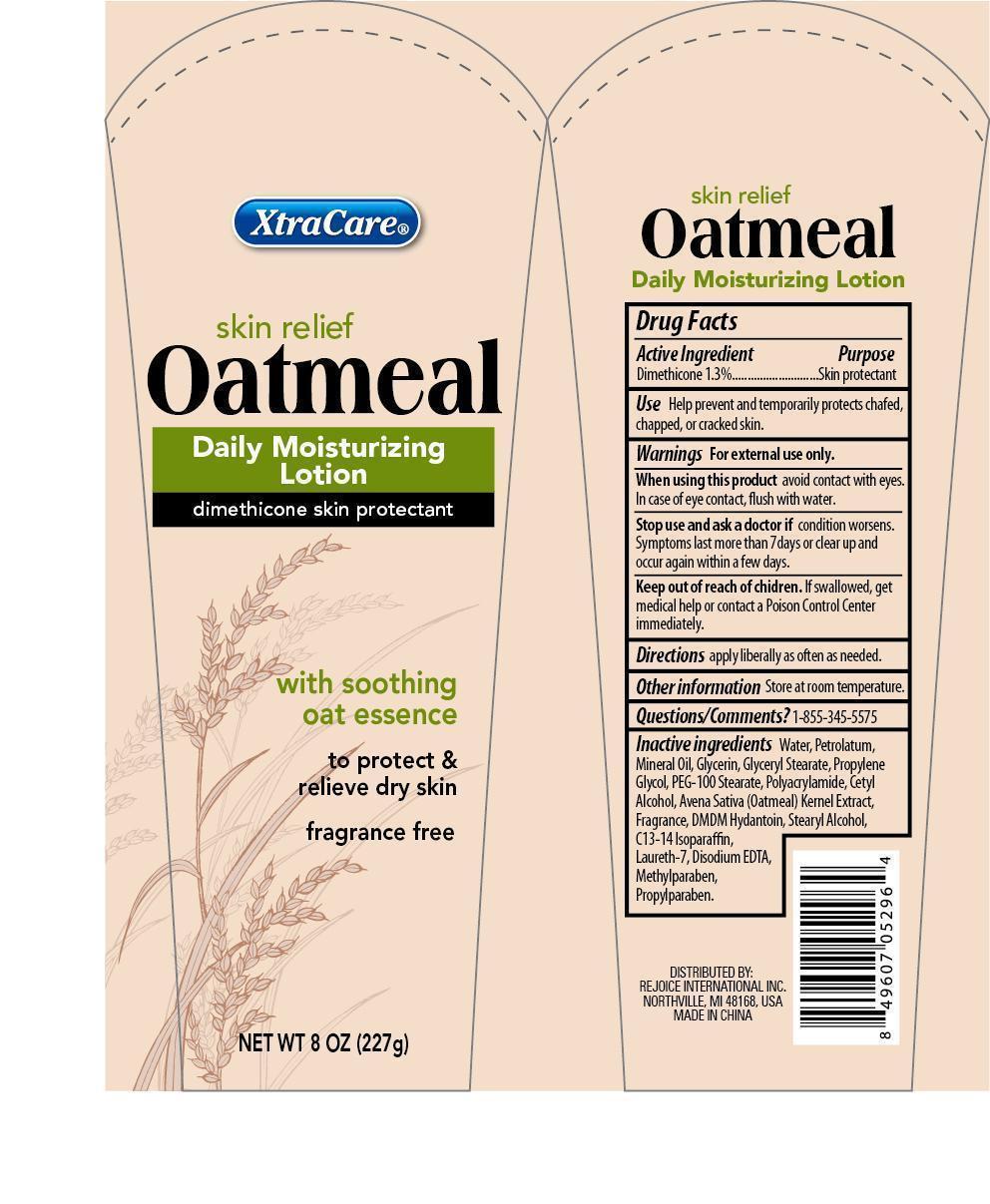 DRUG LABEL: XtraCare Skin Relief Oatmeal Daily Moisturizing
NDC: 57337-054 | Form: LOTION
Manufacturer: Rejoice International
Category: otc | Type: HUMAN OTC DRUG LABEL
Date: 20240228

ACTIVE INGREDIENTS: DIMETHICONE 3 g/227 g
INACTIVE INGREDIENTS: WATER; MINERAL OIL; PETROLATUM; GLYCERIN; GLYCERYL MONOSTEARATE; PROPYLENE GLYCOL; PEG-100 STEARATE; POLYACRYLAMIDE (1500 MW); CETYL ALCOHOL; OAT; DMDM HYDANTOIN; STEARYL ALCOHOL; C13-14 ISOPARAFFIN; LAURETH-7; EDETATE DISODIUM; METHYLPARABEN; PROPYLPARABEN

XtraCare Skin Relief Oatmeal Daily Moisturizing

Active Ingredient Purpose

Dimethicone 1/3% ...... Skin Protectant

PURPOSE

XtraCare Skin Relief Oatmeal Daily Moisturizing Lotion

dimethicone skin protectant

with soothing oat essence

To Protect & Relieve Dry Skin

12 fl oz (354 mL)

Keep out of reach of children. If swallowed, get medical help or contact a Poison Control Center right away.

INDICATIONS AND USAGE

Use help prevent and temporarily protets chafed, chapped, or cracked skin.

Warnings For external use only.

When using this product avoid contact with eyes. In case of eye contact, flush with water.

Stop use and ask a doctor if condition worsens. Symptoms last more than 7 days or clear up and occur again within a few days.

DOSAGE AND ADMINISTRATION

Directions apply liberally as often as needed.

Other information Store at room temperature.

DISTRIBUTED BY:

REJOICE INTERNATIONAL INC.

48325 BINGHAMPTON DR.,

NORTHVILLE, MI 48168 USA

MADE IN CHINA

INACTIVE INGREDIENT

Inactive Ingredients water, paraffinum liquidum, isopropyl myristate, glycerin, glyceryl stearate, propylene glycol, PEG-100 stearate, polyacrylamide, cetyl alcohol, avena sativa kernel extract, fragrance, DMDM hydantoin, stearyl alcohol, c13-14 isoparaffin, laureth-7, disodium EDTA, methylparaben, propylparaben.